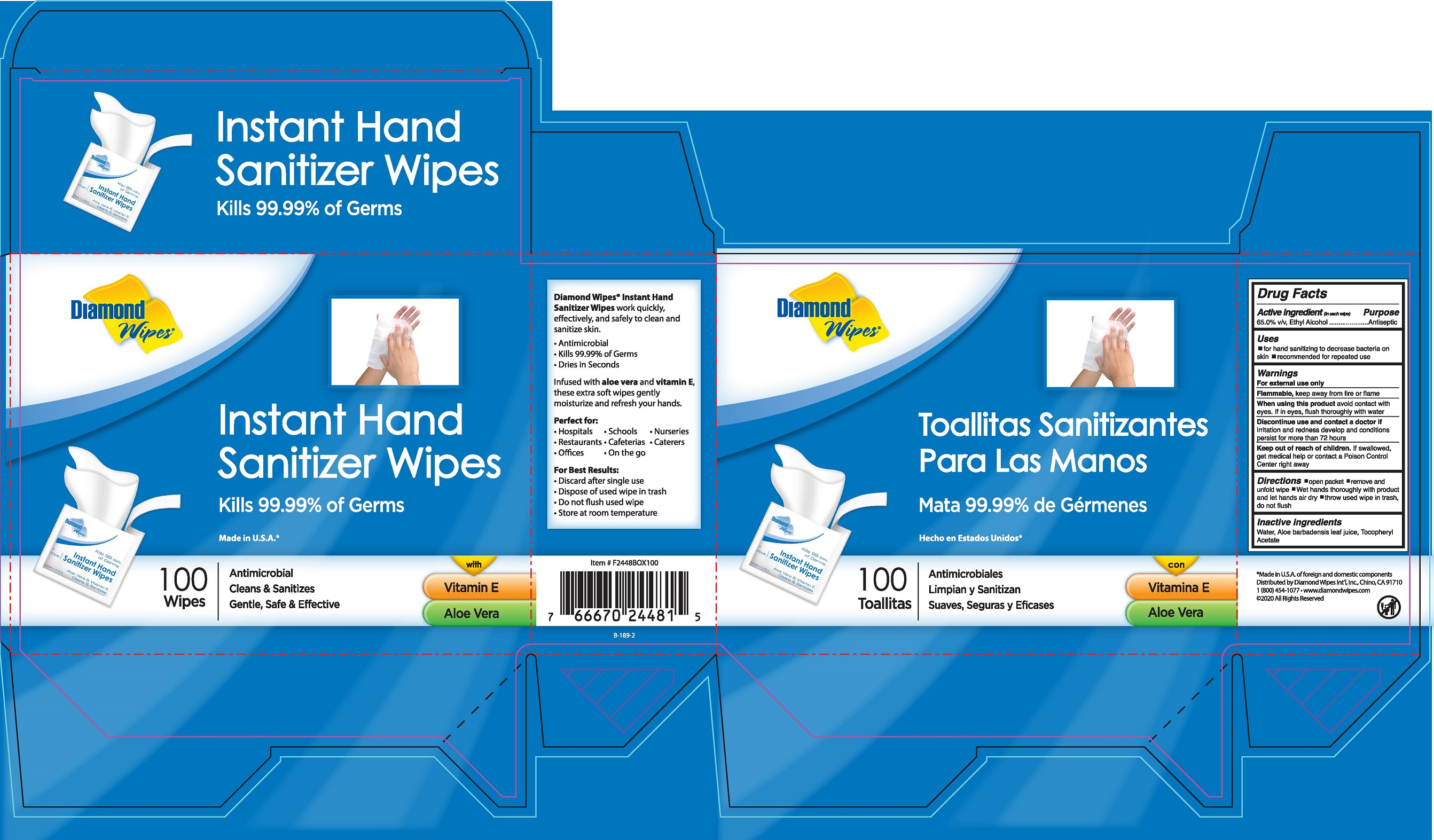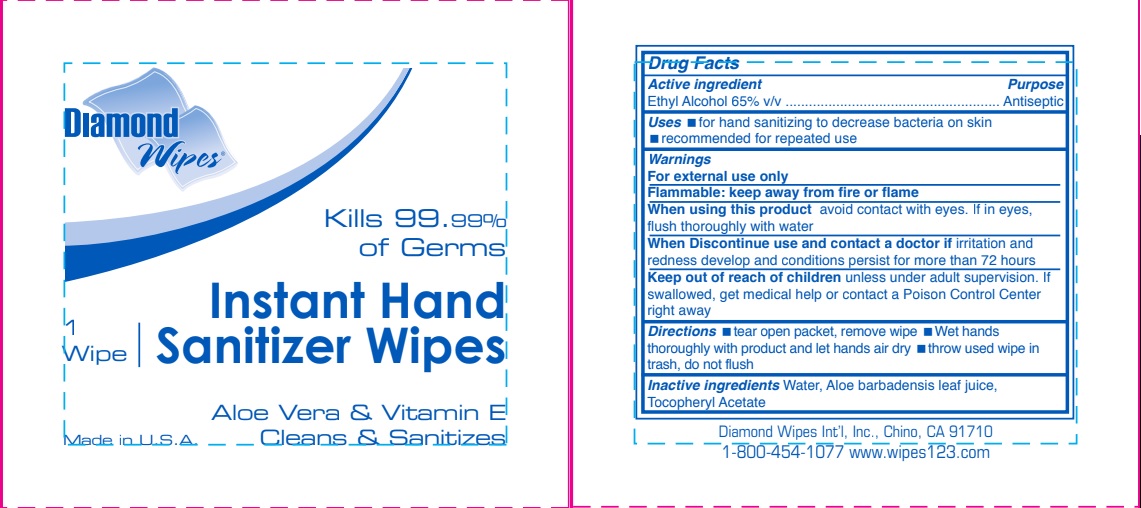 DRUG LABEL: Diamond Wipes Instant Hand Santizer Wipes
NDC: 64709-155 | Form: CLOTH
Manufacturer: Diamond Wipes International, Inc.
Category: otc | Type: HUMAN OTC DRUG LABEL
Date: 20200312

ACTIVE INGREDIENTS: alcohol 65 mL/1 mL
INACTIVE INGREDIENTS: WATER; ALOE VERA LEAF; .ALPHA.-TOCOPHEROL ACETATE, DL-

Active ingredients

Ethyl Alcohol 65% v/v

Purpose

Antiseptic

Uses

- For hand sanitizing to decrease bacteria on skin
- reccomended for repeated use

Warnings

For external use only

Flammable: Keep away from fire or flame

When using this product

avoid contact with eyes. If in eyes, flush thoroughly with water

Discontinue use and contact a doctor

If irritation or redness develops and condition persists for more than 72 hours

Keep out of reach of children

If swallowed get medical help or contact a Poison Control Center right away

Directions

- open packet
- remove and unfold wipes
- wipe hands thoroughly with product and let hands air dry
- throw used wipe in trash
- do not flush

Inactive Ingredients

Water, Aloe Barbadensis leaf juice, tocopheryl acetate

PACKAGE LABEL

Diamond Wipes
Instant Hand Sanitizer wipes
Kills 99.99% of Germs
Clean and Sanitizes
Aloe vera and Vitamin E
Made in USA

Singles

Box